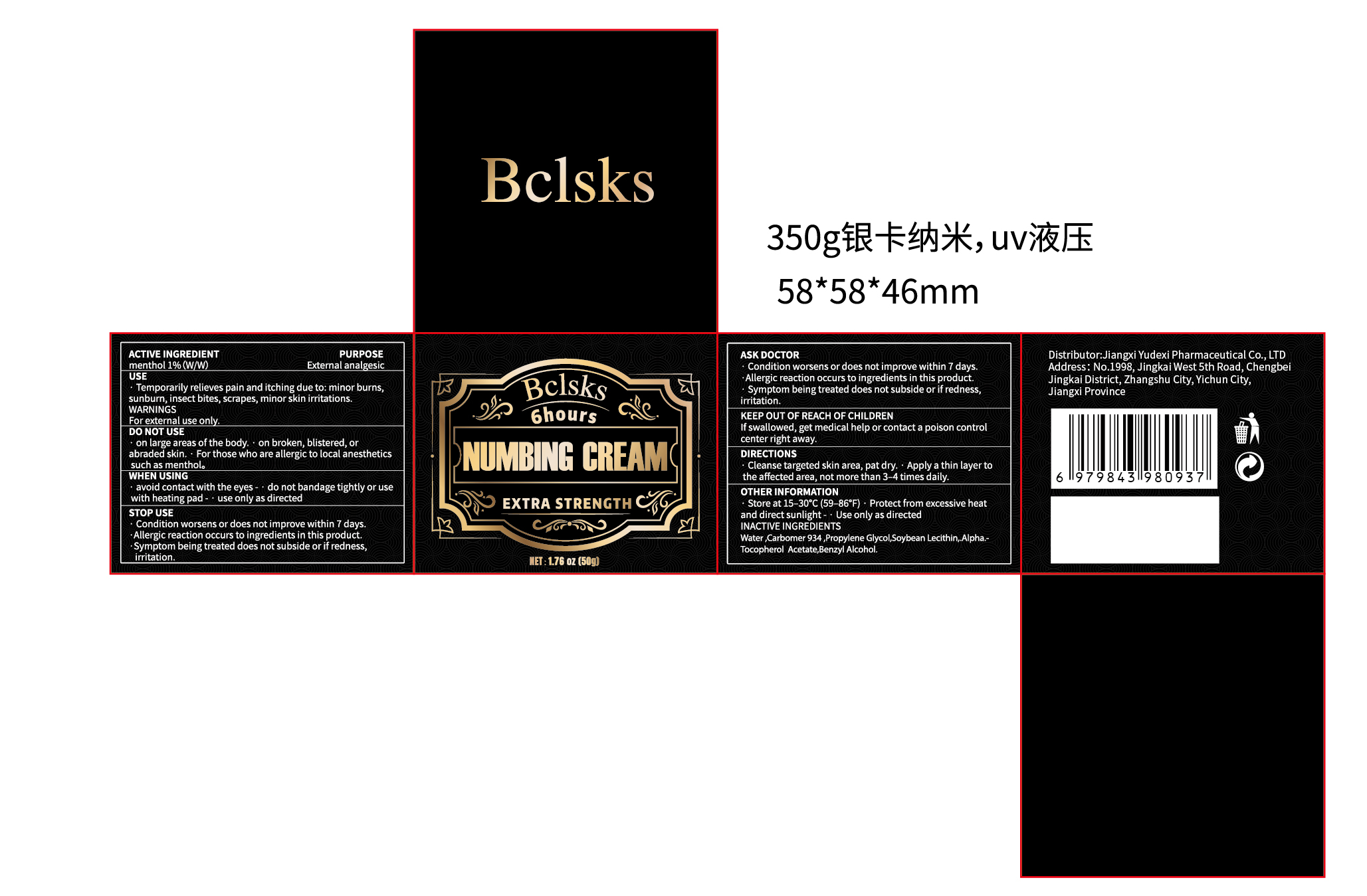 DRUG LABEL: Bclsks  NUMBING
NDC: 85248-043 | Form: CREAM
Manufacturer: Jiangxi Yudexi Pharmaceutical Co., LTD
Category: otc | Type: HUMAN OTC DRUG LABEL
Date: 20260212

ACTIVE INGREDIENTS: MENTHOL 1 g/100 g
INACTIVE INGREDIENTS: BENZYL ALCOHOL; CARBOMER 934; SOYBEAN LECITHIN; PROPYLENE GLYCOL; WATER; .ALPHA.-TOCOPHEROL ACETATE

85248-043

Active Ingredient

menthol 1%（w/w）

Purpose

External analgesic

Use

·Temporarily relieves pain and itching due to: minor burns,sunburn, insect bites, scrapes, minor skin irritations

Warnings

For external use only.

Do not use

·on large areas of the body.·on broken, blistered, or abraded skin. · For those who are allergic to local anesthetics such as menthol.

When Using

·avoid contact with the eyes - ·do not bandage tightly or use with heating pad -· use only as directed

Stop Use

·Condition worsens or does not improve within 7 days.·Allergic reaction occurs to ingredients in this product.·Symptom being treated does not subside or if redness,iritation

Ask Doctor

·Condition worsens or does not improve within 7 days.·Allergic reaction occurs to ingredients in this product.·Symptom being treated does not subside or if redness,iritation

Keep Oot Of Reach Of Children

lf swallowed, get medical help or contact a poison control center right away.

Directions

·Cleanse targeted skin area, pat dry. ·Apply a thin layer to the affected area, not more than 3-4 times daily.

Other information

Store at 15-30°C(59-86°F)·Protect from excessive heat and direct sunlight-· Use only as directed

Inactive ingredients

Water,Carbomer934, propylene Glycol,soybean Lecithin,.Alpha.-Tocopherol Acetate,Benzyl Alcohol.